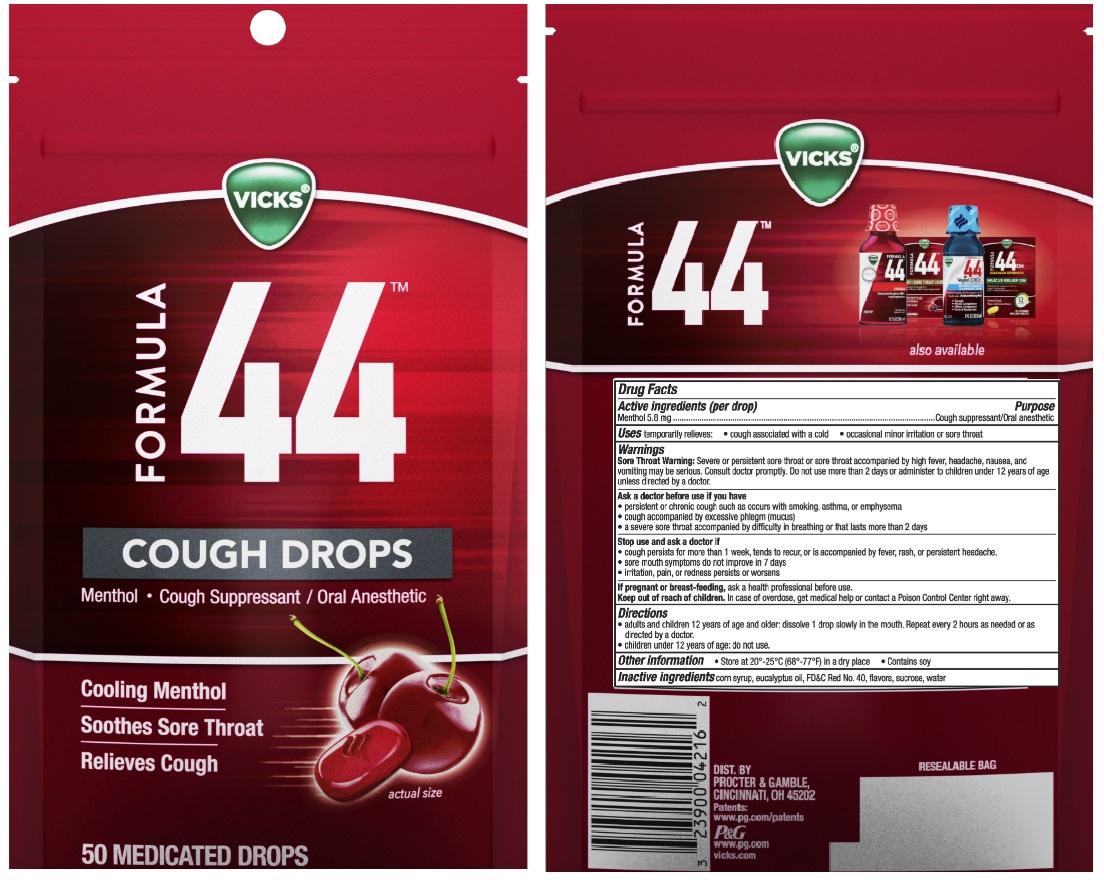 DRUG LABEL: Vicks Formula 44
NDC: 37000-997 | Form: LOZENGE
Manufacturer: The Procter & Gamble Manufacturing Company
Category: otc | Type: HUMAN OTC DRUG LABEL
Date: 20251212

ACTIVE INGREDIENTS: MENTHOL 5.8 mg/1 1
INACTIVE INGREDIENTS: CORN SYRUP; FD&C RED NO. 40; EUCALYPTUS OIL; WATER; SUCROSE

Vicks Formula 44 Cough Drops

Drug Facts

Active ingredient (per drop)

Menthol 5.8 mg

Purpose

Cough suppressant/Oral anesthetic

Uses

temporarily relieves:

- cough associated with a cold
- occasional minor irritation or sore throat

Warnings

Sore Throat Warning:

Severe or persistent sore throat or sore throat accompanied by high fever, headache, nausea, and vomiting may be serious. Consult doctor promptly. Do not use more than 2 days or administer to children under 12 years of age unless directed by doctor.

Ask a doctor before use if you have

- persistent or chronic cough such as occurs with smoking, asthma, or emphysema
- cough accompanied by excessive phlegm (mucus)
- a severe sore throat accompanied by difficulty in breathing or that lasts more than 2 days

Stop use and ask a doctor if

- cough persists for more than 1 week, tends to recur, or is accompanied by fever, rash, or persistent headache.
- sore mouth symptoms do not improve in 7 days
- irritation, pain, or redness persists or worsens

PREGNANCY OR BREAST FEEDING

If pregnant or breast-feeding, ask a health professional before use.

Keep out of reach of children.

OVERDOSAGE

In case of overdose, get medical help or contact a Poison Control Center right away

Directions

- adults and children 12 years and over: dissolve 1 drop slowly in the mouth. Repeat every 2 hours as needed or as directed by a doctor.
- children under 12 years of age: do not use

Other information

- Store at 20°- 25°C (68°-77°F) in a dry place
- Contains soy

Inactive ingredients

corn syrup, eucalyptus oil, FD&C Red No. 40, flavors, sucrose, water

Questions?

1-800-342-6844

DIST. BY
PROCTER & GAMBLE,
CINCINNATI, OH 45202

PRINCIPAL DISPLAY PANEL - 50 Drop Bag

VICKS®

FORMULA 44™

COUGH DROPS

MENTHOL • Cough Suppressant / Oral Anesthetic

Cooling Menthol

Soothes Sore Throat

Relieves Cough

actual size

50 MEDICATED DROPS